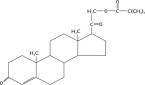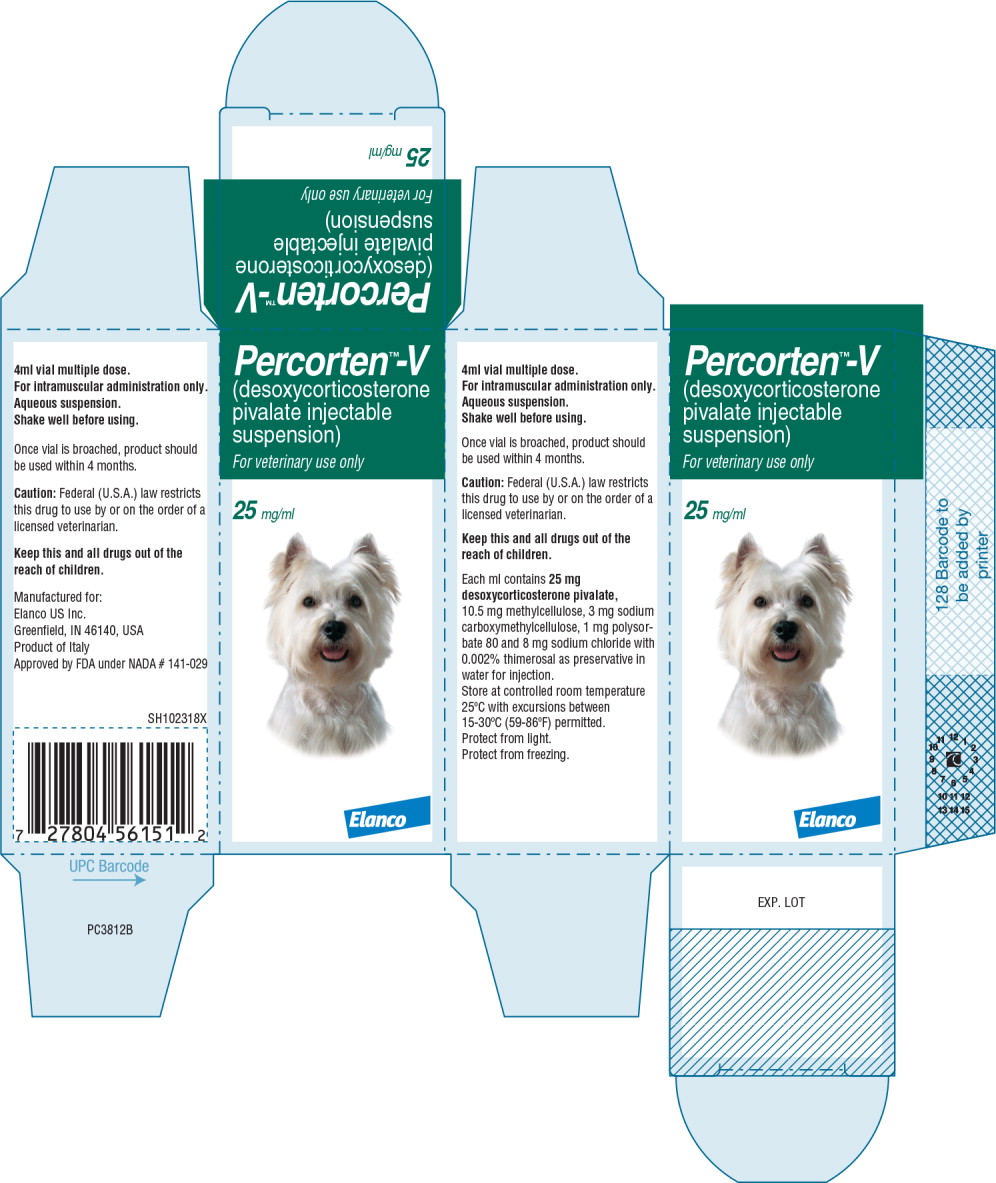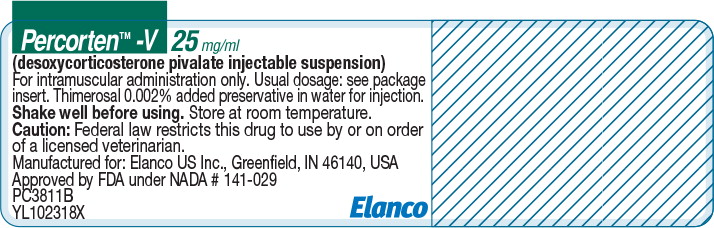 DRUG LABEL: Percorten V
NDC: 58198-5667 | Form: INJECTION, SUSPENSION
Manufacturer: Elanco US Inc.
Category: animal | Type: PRESCRIPTION ANIMAL DRUG LABEL
Date: 20230920

ACTIVE INGREDIENTS: DESOXYCORTICOSTERONE PIVALATE 25 mg/1 mL

Percorten™-V
(desoxycorticosterone pivalate injectable suspension)

CAUTION:

Federal (U.S.A.) law restricts this drug to use by or on the order of a licensed veterinarian.

DESCRIPTION:

The active ingredient in PERCORTEN-V is desoxycorticosterone pivalate (DOCP). It is a mineralocorticoid hormone and an analog of desoxycorticosterone. It is white, odorless, and stable in air. It is practically insoluble in water, sparingly soluble in acetone, slightly soluble in methanol, ether and vegetable oils. The molecular weight is 414.58. It is designated chemically as 21 (2,2-dimethyl-1-oxopropoxy)-pregn-4-ene-3,20-dione. The empirical formula is C26H38O4 and the structural formula is:

PERCORTEN-V is a white aqueous suspension. Each ml contains 25mg desoxycorticosterone pivalate, 10.5mg methylcellulose, 3mg sodium carboxymethylcellulose, 1mg polysorbate 80 and 8mg sodium chloride with 0.002% thimerosal as preservative in water for injection.

CLINICAL PHARMACOLOGY:

Desoxycorticosterone pivalate (DOCP), like other adrenocorticoid hormones, is thought to act by controlling the rate of synthesis of proteins. It reacts with receptor proteins in the cytoplasm to form a steroid-receptor complex. This complex moves into the nucleus, where it binds to chromatin that results in genetic transcription of cellular DNA to messenger RNA. The steroid hormones appear to induce transcription and synthesis of specific proteins which produce the physiologic effects seen after administration.

DOCP is a long-acting ester of desoxycorticosterone acetate (DOCA) which is recognized as having the same qualitative effects as the natural mineralocorticoid hormone aldosterone.

The most important effect of DOCP is to increase the rate of renal tubular absorption of sodium. This effect is seen most intensely in the thick portion of the ascending limb of the loop of Henle. It also increases sodium absorption in the proximal convoluted tubule but this effect is less important in sodium retention. Chloride follows the sodium out of the renal tubule.

Another important effect of DOCP is enhanced renal excretion of potassium. This effect is driven by the resorption of sodium that pulls potassium from the extracellular fluid into the renal tubules, thus promoting potassium excretion.

DOCP also acts to increase extracellular fluid volume. The enhanced retention of sodium, chloride and bicarbonate, creates an osmotic gradient that promotes water absorption from the renal tubules. The extracellular fluid volume is supported. This expands the blood volume and improves the venous return to the heart and cardiac output. The expanded blood volume and increased cardiac output may result in elevated blood pressure. PERCORTEN-V prevents the life threatening hypotensive shock and pre-renal azotemia observed in animals suffering from hypoadrenocorticism.

The effects of PERCORTEN-V on electrolytes and extracellular fluid volume are dependent on a functioning kidney. Animals suffering from hypovolemia, pre-renal azotemia, and inadequate tissue perfusion must be rehydrated with intravenous fluid (saline) therapy, before starting PERCORTEN-V therapy. Primary renal disease should be ruled out before starting PERCORTEN-V therapy.

DOCP is an insoluble ester of desoxycorticosterone. The crystals are injected intramuscularly as a micro-crystalline depot where they slowly dissolve over time.

INDICATION:

For use as replacement therapy for the mineralocorticoid deficit in dogs with primary adrenocortical insufficiency.

WARNING:

Do not use this drug in pregnant dogs. Do not use in dogs suffering from congestive heart disease, severe renal disease or edema.

Keep this and all drugs out of the reach of children. In case of human consumption, contact a physician or Poison Control Center immediately.

PRECAUTIONS:

Some patients are more sensitive to the actions of PERCORTEN-V and may exhibit side effects in an exaggerated degree. Some patients may show signs of hypernatremia or hypokalemia. The dosage of PERCORTEN-V should be reduced in these patients. Concomitant use of PERCORTEN-V with potassium-sparing diuretics, such as spironolactone, may counter the effect of PERCORTEN-V because desoxycorticosterone pivalate and potassium-sparing diurectics exhibit opposing mechanisms of action.

Like other adrenocortical hormones, PERCORTEN-V may cause severe side effects if dosage is too high or prolonged. It may cause polyuria, polydipsia, increased blood volume, edema and cardiac enlargement. Excessive weight gain may indicate fluid retention secondary to sodium retention. PERCORTEN-V should be used with caution in patients with congestive heart disease, edema or renal disease.

ADVERSE REACTIONS (in controlled clinical field studies):

The following adverse reactions have been reported following the use of PERCORTEN-V: depression, polyuria, polydipsia, anorexia, skin and coat changes, diarrhea, vomiting, weakness, weight loss, incontinence, pain on injection and injection site abscess. Some of these effects may resolve with adjustments in dose or interval of PERCORTEN-V or concomitant glucocorticoid medication.

Post-Approval Experience, Rev. 2011:

The following adverse events are based on post-approval adverse drug experience reporting. Not all adverse events are reported to FDA-CVM. It is not always possible to reliably estimate the adverse event frequency or establish a causal relationship to product exposure using this data. The following adverse events are listed in decreasing order of reporting frequency in dogs: depression/lethargy, vomiting, anorexia, polydipsia, polyuria, diarrhea, facial/ muzzle edema, weakness, urticaria and anaphylaxis. Anemia has been reported following DOCP administration. For a complete listing of adverse reactions for desoxycorticosterone pivalate injectable suspension reported to CVM see:

http://www.fda.gov/AnimalVeterinary.

To report adverse effects, access medical information, or obtain additional product information call 1-888-545-5973. For additional information about adverse drug experience reporting for animal drugs, contact FDA at 1-888-FDA-VETS or www.fda.gov/reportanimalae

EFFICACY:

PERCORTEN-V given intramuscularly at the appropriate dose and interval, is effective in replacing the mineralocorticoid deficit in dogs suffering from primary hypoadrenocorticism.

Results of two 75-day clinical studies in dogs with primary hypoadrenocorticism have demonstrated the clinical efficacy of PERCORTEN-V. Each dog received three doses of PERCORTEN-V (on days 0, 25 and 50). The results are summarized below.

 | Clinical Study | Number
 | 01 | 02
Number of Dogs | 49 | 18
Average Diagnostic Values:
Serum Sodium (mEq/L) | 128.4 | 130.72
Serum Potassium (mEq/L) | 7.28 | 7.47
Sodium/Potassium Ratio | 18.09 | 17.86
ACTH Stimulation Test:
Cortisol Resting (μg/dI) | 0.28 | 0.68
Cortisol Post Stimulation (μg/dI) | 0.27 | 1.34
Average PERCORTEN-V Dose (mg/lb):
Day 0 | 0.97 | 0.99
Day 25 | 0.96 | 0.99
Day 50 | 0.94 | 0.97
Concomitant Glucocorticoid (Pred) | 47% | 39%
Sodium/Potassium Ratios
Day 0 | 25.18 | 26.42
Day 14 | 36.36 | –
Day 25 | 29.64 | –
Day 39 | 34.94 | –
Day 50 | 30.33 | –
Day 64 | 35.30 | –
Day 75 | 30.32 | 30.59
% Efficacy Therapy | 96% | 100%

Case Management:^1,2

An accurate diagnosis of primary canine adrenocortical insufficiency is of paramount importance for treatment success and should be established before initiation of PERCORTEN-V therapy. While hyponatremia and hyperkalemia are highly suggestive of adrenocortical insufficiency, they are not pathognomonic. A definitive diagnosis can only be made with an ACTH stimulation test. At diagnosis, classic cases of canine adrenocortical insufficiency may include clinical signs. Those signs are anorexia, lethargy, depression, weakness, vomiting and/or regurgitation, weight loss, diarrhea and collapse, serum sodium values less than 135 mEq/L, serum potassium greater than 6 mEq/L, sodium/potassium ratios below 25:1, plasma or serum cortisol concentration less than 4 μg/dl pre-and-post ACTH administration. Once the diagnosis is made, immediate therapy must be given to normalize electrolyte imbalance, correct hypovolemic shock and re-establish normal homeostasis. Such therapy should include large volumes of intravenous physiologic saline, glucocorticoids (i.e., prednisolone, dexamethasone) at shock doses and PERCORTEN-V. Anemia (normocytic, normochromic) may be present at diagnosis, but not identified due to hemoconcentration. Rapid rehydration may reduce the circulating red blood cell count to life-threatening levels in animals with preexisting anemia. Once the acute crisis has passed, renal and cardiovascular function should return to normal. Patient monitoring and dose adjustments of PERCORTEN-V and glucocorticoids should be instituted at this time (see Dosage).

SAFETY:^3

In a laboratory study the safety of PERCORTEN-V was established in five month old Beagle dogs. PERCORTEN-V was administered IM to 24 Beagles at 0, 2.2, 6.6 or 11 mg/kg of body weight daily over a consecutive 3-day period every 28 days (equivalent to a cumulative monthly dosage of 0, 6.6, 19.8 or 33 mg/kg) for 6 months. This resulted in no mortality or any significant effects on body weight, food consumption, and ophthalmic observations at any dose level. However, polyuria and polydipsia were noted and creatinine concentration decreased (14-89 mg/dl) in the 1X, 3X and 5X groups. Histopathological changes were only observed in the kidneys when PERCORTEN-V was administered at ≥ 6.6 mg/kg. The primary renal lesion consisted of glomerulonephropathy seen in all males at ≥ 6.6 mg/kg, in one female at 6.6 mg/kg, and in all females at 11 mg/kg. Other possible treatment related lesions in the kidney, observed sporadically in the 6.6 and 11.0 mg/kg groups, were tubular hyperplasia, inflammation and tubular dilatation. Glomerulonephropathy may possibly be attributed to the pharmacological effects of the drug although there were no clinical measurements assessed in this study. In conclusion, PERCORTEN-V was well tolerated, when administered at 2.2 mg/kg on three consecutive days in every 28-day period for six months.

DOSAGE:^1,2

In treating canine hypoadrenocorticism, PERCORTEN-V replaces the mineralocorticoid hormones only. Glucocorticoid replacement must be supplied by small daily doses of glucocorticoid hormones (e.g., prednisone or prednisolone) (0.2 – 0.4 mg/kg/day).

Dosage requirements are variable and must be individualized on the basis of the response of the patient to therapy. Begin treatment with PERCORTEN-V at a dose of 1.0 mg per pound of body weight every 25 days. In some patients the dose may be reduced. Serum sodium and potassium levels should be monitored to assure the animal is properly compensated. Most patients are well controlled with a dose range of 0.75 to 1.0 mg per pound of body weight, given every 21 to 30 days.

The well-controlled patient will have normal electrolytes at 14 days after administration or may exhibit slight hyponatremia and hyperkalemia. This needs no additional therapy as long as the patient is active and eating normally. Watch closely for depression, lethargy, vomiting or diarrhea which indicate a probable glucocorticoid deficiency.

At the end of the 25-day dosing interval, the patient should be clinically normal and have normal serum electrolytes. Alternatively, they may have slight hyponatremia and slight hyperkalemia. This constellation of signs indicate that the dosage and dosage interval should not be altered.

If the dog is not clinically normal or serum electrolytes are abnormal, then the dosage interval should be decreased 2-3 days.

Occasionally, dogs on PERCORTEN-V therapy may develop polyuria and polydipsia (PU/PD). This usually indicates excess glucocorticoid, but may also indicate a PERCORTEN-V excess. It is prudent to begin by decreasing the glucocorticoid dose first. If the PU/PD persists, then decrease the dose of PERCORTEN-V without changing the interval between doses.

Please note: Failure to administer glucocorticoids is the most common reason for treatment failure. Signs of glucocorticoid deficiency include depression, lethargy, vomiting and diarrhea. Such signs should be treated with high doses of injectable glucocorticoids (prednisolone or dexamethasone), followed by continued oral therapy 0.2 – 0.4 mg/kg/day. Oral supplementation with salt (NaCI) is not necessary with animals receiving PERCORTEN-V.

Guide to Maintenance Therapy

Starting Dose:

DOCP 1 mg/lb every 25 days
Prednisone 0.2 - 0.4 mg/kg/day

Guides for Adjustment:

Clinical Problem/Solution
Polyuria/Polydipsia

  - decrease prednisone dose first,
  - then decrease DOCP dose,
  - do not change DOCP interval
Depression, lethargy, vomiting or diarrhea
  1. increase prednisone dose
Hyperkalemia, Hyponatremia
  1. decrease DOCP interval 2-3 days

ADMINISTRATION:

Before injection, shake the vial thoroughly to mix the microcrystals with the suspension vehicle. PERCORTEN-V suspension is to be injected intramuscularly. Care should be used to prevent inadvertent intravenous injection, which may cause acute collapse and shock. Such animals should receive immediate therapy for shock with intravenous fluids and glucocorticoids.

Once vial is broached, product should be used within 4 months.

HOW SUPPLIED:

Multiple-Dose Vials, 4 ml, each ml containing 25 mg desoxycorticosterone pivalate (DOCP), 10.5 mg methylcellulose, 3 mg sodium carboxymethylcellulose, 1 mg polysorbate 80, and 8 mg sodium chloride with 0.002% thimerosal added as preservative in water for injection. Packed one vial per carton.

STORAGE:

Store at controlled room temperature 25ºC with excursions between 15-30ºC (59-86ºF) permitted. Protect from light. Protect from freezing.

References:

1. Canine and Feline Endocrinology and Reproduction. Second Edition (1996), E. C. Feldman and R. W. Nelson, W. B.
  Saunders Co., New York and Third Edition (2004) Saunders/Elsevier, USA.
2. Textbook of Veterinary Internal Medicine.
  Fourth Edition, S. J. Ettinger and E. C. Feldman editors, W. B. Saunders Co., New York, 1995.
3. Toxicity of desoxycorticosterone pivalate given at high doses to clinically normal Beagles for six months, E. Chow, W. R. Campbell, J. C. Turnier, R.C. Lynn and K. L. Pavkov, Am. J. Vet. Res. 54(11):1954-1961, 1993.

Manufactured for: Elanco US Inc.
Greenfield, IN 46140, USA
Approved by FDA under NADA # 141-029

PC3810I

Percorten, Elanco and the diagonal bar logo are trademarks of Elanco or its affiliates.

PA102318X

Principal Display Panel - 25 mg/1 mL Carton Label

Percorten ™-V

(desoxycorticosterone
pivalate injectable
suspension)

For veterinary use only

25 mg/ml

Elanco

PRINCIPAL DISPLAY PANEL - 25 MG/1 ML VIAL LABEL

Percorten™-V 25 mg/ml

(desoxycorticosterone pivalate injectable suspension)

For intramuscular administration only. Usual dosage: see package
insert. Thimerosal 0.002% added preservative in water for injection.

Shake well before using. Store at room temperature.

Caution: Federal law restricts this drug to use by or on order
of a licensed veterinarian.

Manufactured for: Elanco US Inc., Greenfield, IN 46140, USA

Approved by FDA under NADA # 141-029

PC3811B

YL102318X

Elanco